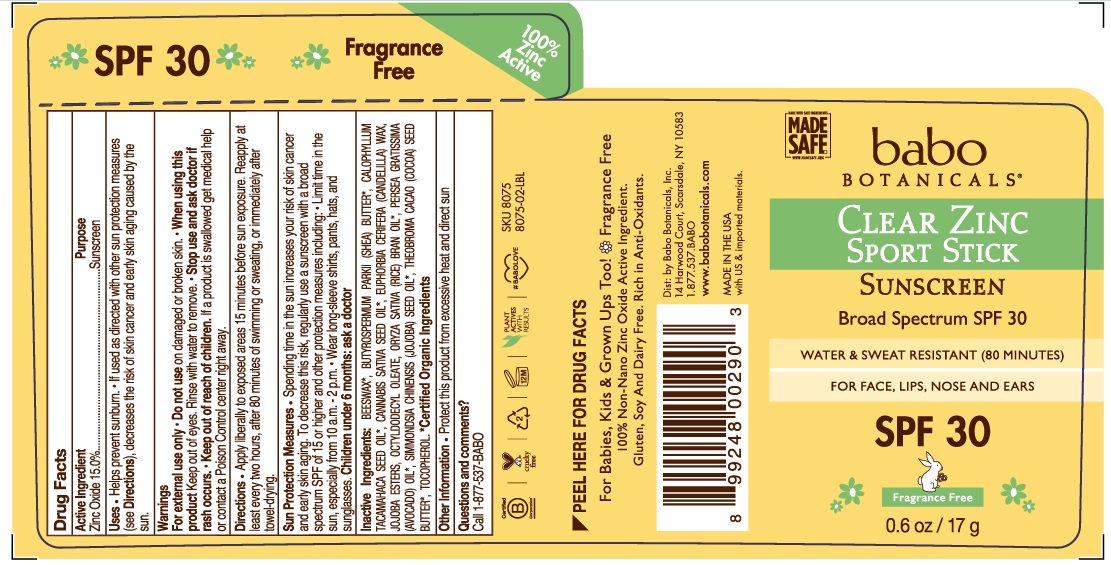 DRUG LABEL: Babo SPF 30 Clear Zinc Fragrance Free Sport
NDC: 79265-8075 | Form: STICK
Manufacturer: Babo Botanicals, Inc.
Category: otc | Type: HUMAN OTC DRUG LABEL
Date: 20241212

ACTIVE INGREDIENTS: ZINC OXIDE 15.326 g/100 g
INACTIVE INGREDIENTS: JOJOBA OIL 7.5 mL/100 g; COCOA BUTTER 3 mL/100 g; CANNABIS SATIVA SEED OIL 0.01 mL/100 g; OCTYLDODECYL OLEATE 8.75 mL/100 g; SHEA BUTTER 1 mL/100 g; CALOPHYLLUM TACAMAHACA SEED OIL 0.01 mL/100 g; RICE BRAN OIL 32.93 mL/100 g; HYDROGENATED JOJOBA OIL, RANDOMIZED 0.47 mL/100 g; WHITE WAX 6 mL/100 g; AVOCADO OIL 15 mL/100 g; TOCOPHEROL 0.5 mL/100 g; CANDELILLA WAX 9.5 mL/100 g

79265-8075 Babo SPF 30 Clear Zinc, Fragrance Free Sport Stick

Active Ingredient

Zinc Oxide 15.0%

Purpose

Sunscreen

Uses

Helps prevent sunburn | If used as directed with other sun protection measures (see Directions), decreases the risk of skin cancer and early skin aging caused by the sun.

Warnings

For external use only

Do not use

on broken or damaged skin

When using this product

keep out of eyes. Rinse with water to remove

Stop use and ask doctor if

rash occurs.

Keep out of reach of children

If product is swallowed get medical help or contact a Poison Control center right away.

Directions

Apply liberally to exposed areas 15 minutes before sun exposure. Reapply at least every two hours, after 80 minutes of swimming or sweating, or immediately after towel-drying.

Sun Protection Measures • Spending time in the sun increases your risk of skin cancer and early skin aging. To decrease this risk, regularly use a sunscreen with a broad spectrum SPF of 15 or higher and other protection measures including: • Limit time in the sun, especially from 10 a.m. - 2 p.m. • Wear long-sleeve shirts, pants, hats, and sunglasses. Children under 6 months: ask a doctor

Inactive Ingredients

BEESWAX*
BUTYROSPERMUM PARKII (SHEA) BUTTER*
CALOPHYLLUM TACAMAHACA SEED OIL*
CANNABIS SATIVA SEED OIL*
EUPHORBIA CERIFERA (CANDELILLA) WAX
JOJOBA ESTERS
OCTYLDODECYL OLEATE
ORYZA SATIVA (RICE) BRAN OIL*
PERSEA GRATISSIMA (AVOCADO) OIL*
SIMMONDSIA CHINENSIS (JOJOBA) SEED OIL*
THEOBROMA CACAO (COCOA) SEED BUTTER*
TOCOPHEROL

*CERTIFIED ORGANIC INGREDIENTS

Other Information

• Protect this product from excessive heat and direct sun

Questions and comments?

Call 1-877-537-BABO